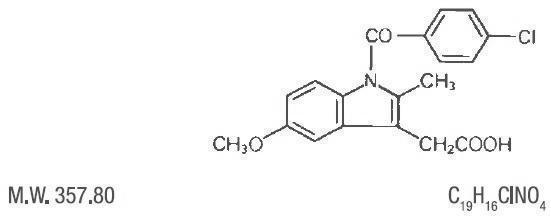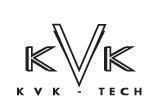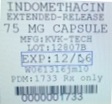 DRUG LABEL: INDOMETHACIN
NDC: 68151-1733 | Form: CAPSULE, EXTENDED RELEASE
Manufacturer: Carilion Materials Management
Category: prescription | Type: HUMAN PRESCRIPTION DRUG LABEL
Date: 20160616

ACTIVE INGREDIENTS: INDOMETHACIN 75 mg/1 1
INACTIVE INGREDIENTS: STARCH, CORN; D&C YELLOW NO. 10; GELATIN; MANNITOL; POVIDONES; SUCROSE; TALC; TITANIUM DIOXIDE

INDOMETHACIN EXTENDED-RELEASE CAPSULES USP 75 mg Rx Only

BOXED WARNING

Cardiovascular Thrombotic Events

• Nonsteroidal anti-inflammatory drugs (NSAIDs) cause an increased risk of serious cardiovascular thrombotic events, including myocardial infarction and stroke, which can be fatal. This risk may occur early in treatment and may increase with duration of use (See and). WARNINGSPRECAUTIONS

• Indomethacin Extended-release Capsules are contraindicated in the setting of coronary artery bypass graft (CABG) surgery (See and). CONTRAINDICATIONSWARNINGS

Gastrointestinal Risk

• NSAIDs cause an increased risk of serious gastrointestinal adverse events including bleeding, ulceration, and perforation of the stomach or intestines, which can be fatal. These events can occur at any time during use and without warning symptoms. Elderly patients are at greater risk for serious gastrointestinal events. (See). WARNINGS

DESCRIPTION:

Indomethacin Extended-release capsules USP 75 cannot be considered a simple analgesic and should not be used in conditions other than those recommended under . INDICATIONS AND USAGE

Indomethacin is a nonsteroidal, anti-inflammatory, indole derivative designated chemically as 1-(4-chlorobenzoyl)-5-methoxy-2-methyl-1 -indole-3-acetic acid. Indomethacin is practically insoluble in water and sparingly soluble in alcohol. It has a pKa of 4.5 and is stable in neutral or slightly acidic media and decomposes in strong alkali. The structural formula is: H

Each extended-release capsule, for oral administration contains 75 mg of indomethacin. In addition, each capsule contains the following inactive ingredients: corn starch, D&C Yellow# 10, gelatin, mannitol, povidone, sucrose, talc, and titanium dioxide.

This product meets USP Drug Release Test 2 Specifications.

CLINICAL PHARMACOLOGY:

Indomethacin is a nonsteroidal drug with anti-inflammatory, antipyretic and analgesic properties. Its mode of action, like that of other anti-inflammatory drugs, is not known. However, its therapeutic action is not due to pituitary-adrenal stimulation.

Indomethacin is a potent inhibitor of prostaglandin synthesis . Concentrations are reached during therapy which have been demonstrated to have an effect as well. Prostaglandins sensitize afferent nerves and potentiate the action of bradykinin in inducing pain in animal models. Moreover, prostaglandins are known to be among the mediators of inflammation. Since indomethacin is an inhibitor of prostaglandin synthesis, its mode of action may be due to a decrease of prostaglandins in peripheral tissues. in vitroin vivo

Indomethacin has been shown to be an effective anti-inflammatory agent, appropriate for long-term use in rheumatoid arthritis, ankylosing spondylitis, and osteoarthritis.

Indomethacin affords relief of symptoms; it does not alter the progressive course of the underlying disease.

Indomethacin suppresses inflammation in rheumatoid arthritis as demonstrated by relief of pain, and reduction of fever, swelling and tenderness. Improvement in patients treated with indomethacin for rheumatoid arthritis has been demonstrated by a reduction in joint swelling, average number of joints involved, and morning stiffness; by increased mobility as demonstrated by a decrease in walking time; and by improved functional capability as demonstrated by an increase in grip strength.

Indomethacin has been reported to diminish basal and CO stimulated cerebral blood flow in healthy volunteers following acute oral and intravenous administration. In one study, after one week of treatment with orally administered indomethacin, this effect on basal cerebral blood flow had disappeared. The clinical significance of this effect has not been established.2

Indomethacin Extended-release Capsules USP 75 mg are designed to release 25 mg of drug initially and the remaining 50 mg over approximately 12 hours (90% of dose absorbed by 12 hours). Plasma concentrations of indomethacin fluctuate less and are more sustained following administration of Indomethacin Extended-release Capsules USP 75 mg than following administration of 25 mg indomethacin capsules given at 4 to 6 hour Intervals. In multiple-dose comparisons, the mean daily steady state plasma level of indomethacin attained with daily administration of Indomethacin Extended-release Capsules USP 75 mg was indistinguishable from that following indomethacin 25 mg capsules given at 0, 6, and 12 hours daily. However, there was a significant difference in indomethacin plasma levels between the two dosage regimens especially after 12 hours.

Controlled clinical studies of safety and efficacy in patients with osteoarthritis have shown that one capsule of Indomethacin Extended-release Capsules USP 75 mg was clinically comparable to one 25 mg indomethacin capsule t.i.d.; and in controlled clinical studies in patients with rheumatoid arthritis, one capsule of Indomethacin Extended-release Capsules USP 75 mg taken in the morning and one in the evening were clinically indistinguishable from one 50 mg capsule of indomethacin t.i.d.

Indomethacin is eliminated via renal excretion, metabolism, and biliary excretion. Indomethacin undergoes appreciable enterohepatic circulation. The mean half-life of indomethacin is estimated to be about 4.5 hours. With a typical therapeutic regimen of 25 or 50 mg t.i.d., the steady state plasma concentrations of indomethacin are an average 1.4 times those following the first dose.

Indomethacin exists in the plasma as the parent drug and its desmethyl, desbenzoyl, and desmethyl-desbenzoyl metabolites, all in the unconjugated form. About 60 percent of an oral dosage is recovered in urine as drug and metabolites (26 percent as indomethacin and its glucuronide), and 33 percent is recovered in feces (1.5 percent as indomethacin).

About 99% of indomethacin is bound to protein in plasma over the expected range of therapeutic plasma concentrations. Indomethacin has been found to cross the blood-brain barrier and the placenta.

INDICATIONS AND USAGE:

Carefully consider the potential benefits and risks of Indomethacin Extended-release Capsules USP 75 mg and other treatment options before deciding to use Indomethacin Extended-release Capsules USP 75 mg. Use the lowest effective dose for the shortest duration consistent with individual patient treatment goals (See). WARNINGS

Indomethacin Extended-release Capsules USP 75 mg has been found effective in active stages of the following:

1. Moderate to severe rheumatoid arthritis including acute flares of chronic disease.

2. Moderate to severe ankylosing spondylitis.

3. Moderate to severe osteoarthritis.

4. Acute painful shoulder (bursitis and/or tendinitis).

Indomethacin Extended-release Capsules USP 75 mg are not recommended for the treatment of acute gouty arthritis.

Indomethacin may enable the reduction of steroid dosage in patients receiving steroids for the more severe forms of rheumatoid arthritis. In such instances the steroid dosage should be reduced slowly and the patients followed very closely for any possible adverse effects.

The use of indomethacin in conjunction with aspirin or other salicylates is not recommended. Controlled clinical studies have shown that the combined use of indomethacin and aspirin does not produce any greater therapeutic effect than the use of indomethacin alone. Furthermore, in one of these clinical studies, the incidence of gastrointestinal side effects was significantly increased with combined therapy (See). PRECAUTIONS, Drug Interactions

CONTRAINDICATIONS:

Indomethacin Extended-release Capsules are contraindicated in patients with known hypersensitivity to Indomethacin.

Indomethacin Extended-release Capsules should not be given to patients who have experienced asthma, urticaria, or allergic-type reactions after taking aspirin or other NSAIDs. Severe, rarely fatal, anaphylactic-like reactions to NSAIDs have been reported in such patients (See , and). WARNINGSPRECAUTIONS - Preexisting Asthma

In the setting of coronary artery bypass graft (CABG) surgery (See). WARNINGS

PRECAUTIONS:

General

Indomethacin Extended-release Capsules cannot be expected to substitute for corticosteroids or to treat corticosteroid insufficiency. Abrupt discontinuation of corticosteroids may lead to disease exacerbation. Patients on prolonged corticosteroid therapy should have their therapy tapered slowly if a decision is made to discontinue corticosteroids.

The pharmacological activity of Indomethacin Extended-release Capsules in reducing [fever and] inflammation may diminish the utility of these diagnostic signs in detecting complications of presumed noninfectious, painful conditions.

Hepatic Effects

Borderline elevations of one or more liver tests may occur in up to 15% of patients taking NSAIDs including Indomethacin Extended-release Capsules. These laboratory abnormalities may progress, may remain unchanged, or may be transient with continuing therapy. Notable elevations of ALT or AST (approximately three or more times the upper limit of normal) have been reported in approximately 1% of patients in clinical trials with NSAIDs. In addition, rare cases of hepatic reactions, including jaundice and fatal fulminant hepatitis, liver necrosis and hepatic failure, some of them with fatal outcomes have been reported.

A patient with symptoms and/or signs suggesting liver dysfunction, or in whom an abnormal liver test has occurred, should be evaluated for evidence of the development of a more severe hepatic reaction while on therapy with Indomethacin Extended-release Capsules. If clinical signs and symptoms consistent with liver disease develop, or if systemic manifestations occur (e.g., eosinophilia, rash, etc.), Indomethacin Extended-release Capsules should be discontinued.

Hematological Effects

Anemia is sometimes seen in patients receiving NSAIDs, including Indomethacin Extended-release Capsules. This may be due to fluid retention, occult or gross GI blood loss, or an incompletely described effect upon erythropoiesis. Patients on long-term treatment with NSAIDs, including Indomethacin Extended-release Capsules, should have their hemoglobin or hematocrit checked if they exhibit any signs or symptoms of anemia.

NSAIDs inhibit platelet aggregation and have been shown to prolong bleeding time in some patients. Unlike aspirin, their effect on platelet function is quantitatively less, of shorter duration, and reversible. Patients receiving Indomethacin Extended-release Capsules who may be adversely affected by alterations in platelet function, such as those with coagulation disorders or patients receiving anticoagulants, should be carefully monitored.

Preexisting Asthma

Patients with asthma may have aspirin-sensitive asthma. The use of aspirin in patients with aspirin-sensitive asthma has been associated with severe bronchospasm which can be fatal. Since cross reactivity, including bronchospasm, between aspirin and other nonsteroidal anti-inflammatory drugs has been reported in such aspirin-sensitive patients, Indomethacin Extended-release Capsules should not be administered to patients with this form of aspirin sensitivity and should be used with caution in patients with preexisting asthma.

Information for Patients

Patients should be informed of the following information before initiating therapy with a NSAID and periodically during the course of ongoing therapy. Patients should also be encouraged to read the NSAID Medication Guide that accompanies each prescription dispensed.

1. Cardiovascular Thrombotic Events

Advise patients to be alert for the symptoms of cardiovascular thrombotic events, including chest pain, shortness of breath, weakness, or slurring of speech, and to report any of these symptoms to their health care provider immediately (See). WARNINGS

2. Indomethacin Extended-release Capsules, like other NSAIDs, can cause GI discomfort and, rarely, serious GI side effects, such as ulcers and bleeding, which may result in hospitalization and even death. Although serious GI tract ulcerations and bleeding can occur without warning symptoms, patients should be alert for the signs and symptoms of ulcerations and bleeding, and should ask for medical advice when observing any indicative sign or symptoms including epigastric pain, dyspepsia, melena, and hematemesis. Patients should be apprised of the importance of this follow-up (See). WARNINGS, Gastrointestinal Effects: Risk of Ulceration, Bleeding, and Perforation

3. Indomethacin Extended-release Capsules, like other NSAIDs, can cause serious skin side effects such as exfoliative dermatitis, SJS, and TEN, which may result in hospitalization and even death. Although serious skin reactions may occur without warning, patients should be alert for the signs and symptoms of skin rash and blisters, fever, or other signs of hypersensitivity such as itching, and should ask for medical advice when observing any indicative signs or symptoms. Patients should be advised to stop the drug immediately if they develop any type of rash and contact their physicians as soon as possible.

4. Heart Failure And Edema

Advise patients to be alert for the symptoms of congestive heart failure including shortness of breath, unexplained weight gain, or edema and to contact their healthcare provider if such symptoms occur (See). WARNINGS

5. Patients should be informed of the warning signs and symptoms of hepatotoxicity (e.g., nausea, fatigue, lethargy, pruritus, jaundice, right upper quadrant tenderness, and "flu-like" symptoms). If these occur, patients should be instructed to stop therapy and seek immediate medical therapy.

6. Patients should be informed of the signs of an anaphylactoid reaction (e.g., difficulty breathing, swelling of the face or throat). If these occur, patients should be instructed to seek immediate emergency help (See). WARNINGS

7. In late pregnancy, as with other NSAIDs, Indomethacin Extended-release Capsules should be avoided because it will cause premature closure of the ductus arteriosus.

Laboratory Tests

Because serious GI tract ulcerations and bleeding can occur without warning symptoms, physicians should monitor for signs or symptoms of GI bleeding. Patients on long-term treatment with NSAIDs, should have their CBC and a chemistry profile checked periodically. If clinical signs and symptoms consistent with liver or renal disease develop, systemic manifestations occur (e.g., eosinophilia, rash, etc.) or if abnormal liver tests persist or worsen, Indomethacin Extended-release Capsules should be discontinued.

Drug Interactions

ACE-Inhibitors

Reports suggest that NSAIDs may diminish the antihypertensive effect of ACE-inhibitors. This interaction should be given consideration in patients taking NSAIDs concomitantly with ACE-inhibitors.

Aspirin

When Indomethacin Extended-release Capsules are administered with aspirin, its protein binding is reduced, although the clearance of free Indomethacin Extended-release Capsules is not altered. The clinical significance of this interaction is not known; however, as with other NSAIDs, concomitant administration of Indomethacin and aspirin is not generally recommended because of the potential of increased adverse effects.

Furosemide

Clinical studies, as well as post marketing observations, have shown that Indomethacin Extended-release Capsules can reduce the natriuretic effect-of furosemide and thiazides in some patients. This response has been attributed to inhibition of renal prostaglandin synthesis. During concomitant therapy with NSAIDs, the patient should be observed closely for signs of renal failure (See), as well as to assure diuretic efficacy. WARNINGS, Renal Effects

Lithium

NSAIDs have produced an elevation of plasma lithium levels and a reduction in renal lithium clearance. The mean minimum lithium concentration increased 15% and the renal clearance was decreased by approximately 20%. These effects have been attributed to inhibition of renal prostaglandin synthesis by the NSAID. Thus, when NSAIDs and lithium are administered concurrently, subjects should be observed carefully for signs of lithium toxicity.

Methotrexate

NSAIDs have been reported to competitively inhibit methotrexate accumulation in rabbit kidney slices. This may indicate that they could enhance the toxicity of methotrexate. Caution should be used when NSAIDs are administered concomitantly with methotrexate.

Warfarin

The effects of warfarin and NSAIDs on GI bleeding are synergistic, such that users of both drugs together have a risk of serious GI bleeding higher than users of either drug alone.

Drug/Laboratory Test Interactions

Only if positive interactions have been observed. (See 201.57 (f)(4)(N))

Carcinogensis, Mutagenesis, Impairment of Fertility

Usually only if significant findings have been observed. (See 201.57 (f)(5))

Prenancy

Teratogenic Effects, Pregnancy Category C.

Reproductive studies conducted in rats and rabbits have not demonstrated evidence of developmental abnormalities. However, animal reproduction studies are not always predictive of human response. There are no adequate and well-controlled studies in pregnant women.

Nonteratogenic Effects

Because of the known effects of nonsteroidal anti-inflammatory drugs on the fetal cardiovascular system (closure of ductus arteriosus), use during pregnancy (particularly late pregnancy) should be avoided.

Labor and Delivery

In rat studies with NSAIDs, as with other drugs known to inhibit prostaglandin synthesis, an increased incidence of dystocia, delayed parturition, and decreased pup survival occurred. The effects of Indomethacin Extended-release Capsules on labor and delivery in pregnant women are unknown.

Nursing Mothers

It is not known whether this drug is excreted in human milk. Because many drugs are excreted in human-milk and because of the potential for serious adverse reactions in nursing infants from Indomethacin Extended-release Capsules, a decision should be made whether to discontinue nursing or to discontinue the drug, taking into account the importance of the drug to the mother.

Pediatric Use

Safety and effectiveness in pediatric patients below the age of 14 years old have not been established.

Geriatric Use

As with any NSAIDs, caution should be exercised in treating the elderly (65 years and older).

ADVERSE REACTIONS:

The adverse reactions for indomethacin capsules listed in the following table have been arranged into two groups: 1) incidence greater than 1% and (2) incidence less than 1%. The incidence for group (1) was obtained from 33 double-blind controlled clinical trials reported in the literature (1,092 patients). The incidence for group (2) was based on reports in clinical trials, in the literature, and on voluntary reports since marketing. The probability of a causal relationship exists between indomethacin and these adverse reactions, some of which have been reported only rarely.

In controlled clinical trials, the incidence of adverse reactions to Indomethacin Extended-release Capsules USP 75 mg and equal 24-hour doses of indomethacin capsules were similar.

Incidence great than 1% | Incidence less than 1%

GASTROINTESTINAL

nausea* with or without vomiting

dyspepsia* (including indigestion, heartburn and epigastric pain)

diarrhea

abdominal distress or pain constipation

anorexia

bloating (includes distention)

flatulence

peptic ulcer

gastroenteritis

rectal bleeding

proctitis

single or multiple ulcerations, including perforation and hemorrhage of the esophagus, stomach,duodenum or small and large intestines

Intestinal ulceration associated with stenosis and obstruction

gastrointestinal bleeding without obvious ulcer formation and perforation of pre-existing sigmoid lesions (diverticulum, carcinoma, etc.) development of ulcerative colitis and regional ileitisulcerative stomatitis

toxic hepatitis and jaundice (some fatal cases have been reported)

CENTRAL NERVOUS SYSTEM

headache (11.7%)

dizziness*

vertigo

somnolence

depression and fatigue

including malaise and listlessness)

anxiety (includes nervousness)

muscle weakness

involuntary muscle movemets insomnia

muzziness

psychic disturbances including psychotic episodes

mental confussion

drowsiness

light-headedness

syncope

paresthesia

aggravation of epilepsy and parkinsonism

depersonalization

coma

peripheral neuropathy convulsions dysarthria

SPECIAL SENSES

tinnitus | ocular-corneal deposits and retinal disturbances, including those of macula, have been reported in some patients on prolonged therapy with indomethacin | blurred vision; diplopia; hearing disturbances, deafness

CARDIOVASCULAR

none | hypertension; hypotension; tachycardia; chest pain | congestive heart failure; arrhythmia; palpitations

METABOLIC

none | edema; weight gain; fluid retention; flushing or sweating | hyperglycemia; glycosuria hyperkalemia

INTEGUMENTARY

none | pruritus; rash; urticaria; petechiae or ecchymosis | exfoliative dermatitis; erythema nodosum; loss of hair; Stevens-Johnson syndrome; erythema multiforme; toxic epidermal necrolysis

HEMATOLOGIC

none | leukopenia; bone marrow depression; anemia secondary to obvious or occult gastrointestinal; bleeding | aplastic anemia; hemolytic anemia; agranulocytosis; thrombocytopenic; purpura; disseminated; intravascular; coagulation

HYPERSENSITIVITY

none | acute anaphylaxis; acute respiratory; distress; rapid fall in blood; pressure resembling a shock; -like state angioedema | dyspnea; asthma; purpura; angiitis; pulmonary edema; fever

GENITOURINARY

none | hematuria; vaginal bleeding; proteinuria; nephrotic syndrome; interstitial nephritis | BUN elevation; renal insufficiency; including renal failure

MISCELLANEOUS

none | epistaxis; breast changes,; including enlargement and; tenderness, or gynecomastia

* Reactions occurring in 3% to 9% of patients treated with indomethacin. (Those reactions occurring in less than 3% of the patients are unmarked.)

Other reactions have been reported but occurred under circumstances where a causal relationship could not be established. However, in these rarely reported events, the possibility cannot be excluded. Therefore, these observations are being listed to serve as alerting information to physicians: Causal Relationship Unknown:

A rare occurrence of fulminant necrotizing fasciitis, particularly in association with Group A β-hemolytic streptococcus, has been described in persons treated with nonsteroidal anti-inflammatory agents, including indomethacin, sometimes with fatal outcome (See also). PRECAUTIONS,General

: Thrombophlebitis.
Cardiovascular

: Although there have been several reports of leukemia, the supporting information is weak.
Hematologic

: Urinary frequency.
Genitourinary

OVERDOSAGE:

The following symptoms may be observed following overdosage: nausea, vomiting, intense headache, dizziness, mental confusion, disorientation, or lethargy. There have been reports of paresthesias, numbness, and convulsions.

Treatment is symptomatic and supportive. The stomach should be emptied as quickly as possible if the ingestion is recent. If vomiting has not occurred spontaneously, the patient should be induced to vomit with syrup of ipecac. If the patient is unable to vomit, gastric lavage should be performed. Once the stomach has been emptied, 25 or 50 g of activated charcoal may be given. Depending on the condition of the patient, close medical observation and nursing care may be required. The patient should be followed for several days because gastrointestinal ulceration and hemorrhage have been reported as adverse reactions of indomethacin. Use of antacids may be helpful.

The oral LD of indomethacin in mice and rats (based on 14 day mortality response) was 50 and 12 mg/kg, respectively.50

DOSAGE AND ADMINISTRATION:

Carefully consider the potential benefits and risks of Indomethacin Extended-release Capsules and other treatment options before deciding to use Indomethacin Extended-release Capsules. Use the lowest effective dose for the shortest duration consistent with individual patient treatment goals (See). WARNINGS

Indomethacin Extended-release Capsules USP 75 mg are available for oral use. Indomethacin Extended-release Capsules USP 75 mg can be administered once a day and can be substituted for indomethacin 25 mg capsules t.i.d. However, there will be significant difference between the two dosage regimens in indomethacin blood levels, especially after 12 hours (See). In addition, Indomethacin Extended-release Capsules USP 75 mg b.i.d. can be substituted for indomethacin 50 mg capsules t.i.d. Indomethacin Extended-release Capsules USP 75 mg may be substituted for all the indications of indomethacin capsules except acute gouty arthritis.
CLINICAL PHARMACOLOGY

Adverse reactions appear to correlate with the size of the dose of indomethacin in most patients, but not all. Therefore, every effort should be made to determine the smallest effective dosage for the individual patient.

Always give Indomethacin Extended-release Capsules USP 75 mg with food, immediately after meals, or with antacids to reduce gastric irritation.

Indomethacin Extended-release Capsules USP 75 mg ordinarily should not be prescribed for children 14 years of age and under (See).
Pediatric Use: WARNINGS

Dosage Recommendations for Active Stages of the Following:
Adult Use:

1. Moderate to severe rheumatoid arthritis, including acute flares of chronic disesase; moderate to severe ankylosing spondylitis; and moderate to severe osteoarthritis.

The following information is provided as background only and refers to immediate-release indomethacin capsules (25 mg or 50 mg):

Suggested Dosage:

The following recommendations on dosing pertain to immediate-release indomethacin capsules USP, and provide important information regarding the dosage and administration of indomethacin. The prescriber should be aware of this information when considering and prescribing Indomethacin Extended-release Capsules USP 75 mg.

Indomethacin capsules 25 mg b.i.d. or t.i.d. If this is well tolerated, increase the daily dosage by 25 or 50 mg, if required by continuing symptoms, at weekly intervals until a satisfactory response is obtained or until a total daily dose of 150-200 mg is reached. DOSES ABOVE THIS AMOUNT GENERALLY DO NOT INCREASE THE EFFECTIVENESS OF THE DRUG.

In patients who have persistent night pain and/or morning stiffness, the giving of a large portion, up to a maximum of 100 mg, of the total daily dose at bedtime, either orally or by rectal suppositories, may be helpful in affording relief. The total daily dose should not exceed 200 mg. In acute flares of chronic rheumatoid arthritis, it may be necessary to increase the dosage by 25 mg or, if required, by 50 mg daily.

The following information refers to Indomethacin Extended-release Capsules USP 75 mg:

If Indomethacin Extended-release Capsules USP 75 mg are used for initiating indomethacin treatment, one capsule daily should be the usual starting dose in order to observe patient tolerance since 75 mg per day is the maximum recommended starting dose for indomethacin (see above). If Indomethacin Extended-release Capsules USP 75 mg are used to increase the daily dose, patients should be observed for possible signs and symptoms of intolerance since the daily increment will exceed the daily increment recommended for other dosage forms. For patients who require 150 mg of indomethacin per day and have demonstrated acceptable tolerance, Indomethacin Extended-release Capsules USP 75 mg may be prescribed as one capsule twice daily.

If minor adverse effects develop as the dosage is increased, reduce the dosage rapidly to a tolerated dose and OBSERVE THE PATIENT CLOSELY.

If severe adverse reactions occur, STOP THE DRUG. After the acute phase of the disease is under control, an attempt to reduce the daily dose should be made repeatedly until the patient is receiving the smallest effective dose or the drug is discontinued.

Careful instructions to, and observations of, the individual patient are essential to the prevention of serious, irreversible, including fatal, adverse reactions.

As advancing years appear to increase the possibility of adverse reactions, Indomethacin Extended-release Capsules should be used with greater care in the aged.

2. Acute painful shoulder (bursitis and/or tendinitis): Initial Dose: 75 mg to 150mg daily. When 150 mg is prescribed, give as one capsule twice daily.

The drug should be discontinued after the signs and symptoms of inflammation have been controlled for several days. The usual course of therapy is 7 to 14 days.

HOW SUPPLIED:

NDC:68151-1733-8 in a BOTTLE of 1 CAPSULE, EXTENDED RELEASES

Medication Guide for Nonsteroidal Anti-Inflammatory Drugs (NSAIDs)

What is the most important information I should know about medicines called Non-steroidal Anti-inflammatory Drugs (NSAIDs)?

NSAIDs can cause serious side effects, including:

• This risk may happen early in treatment and may increase: Increased risk of a heart attack or stroke that can lead to death.

° with increasing doses of NSAIDs

° with longer use of NSAIDs

Do not take NSAIDs right before or after a heart surgery called a "coronary artery bypass graft (CABG)’’.

Avoid taking NSAIDs after a recent heart attack, unless your healthcare provider tells you to. You may have an increased risk of another heart attack if you take NSAIDs after a recent heart attack.

• Increased risk of bleeding, ulcers, and tears (perforation) of the esophagus (tube leading from the mouth to the stomach), stomach and intestines:

° anytime during use

° without warning symptoms

° that may cause death

The risk of getting an ulcer or bleeding increases with:

° past history of stomach ulcers, or stomach or intestinal bleeding with use of NSAIDs

° taking medicines called "corticosteroids", "anticoagulants", "SSRIs", or "SNRIs"

° increasing doses of NSAIDs

° longer use of NSAIDs

° smoking

° drinking alcohol

° older age

° poor health

° advanced liver disease

° bleeding problems

NSAIDs should only be used:

° exactly as prescribed

° at the lowest dose possible for your treatment

° for the shortest time needed

What are NSAIDs?

NSAIDs are used to treat pain and redness, swelling, and heat (inflammation) from medical conditions such as different types of arthritis, menstrual cramps, and other types of short-term pain.

Who should not take NSAIDs?

Do not take NSAIDs:

• if you have had an asthma attack, hives, or other allergic reaction with aspirin or any other NSAIDs.

• right before or after heart bypass surgery.

Before taking NSAIDS, tell your healthcare provider about all of your medical conditions, including if you:

•have liver or kidney problems

• have high blood pressure

• have asthma

• are pregnant or plan to become pregnant. Talk to your healthcare provider if you are considering taking NSAIDs during pregnancy. You should not take NSAIDs after 29 weeks of pregnancy.

• are breastfeeding or plan to breast feed.

NSAIDs and some other medicines can interact with each other and cause serious side effects. Tell your healthcare provider about all of the medicines you take, including prescription or over-the-counter medicines, vitamins or herbal supplements. Do not start taking any new medicine without talking to your healthcare provider first.

What are the possible side effects of NSAIDs?

NSAIDs can cause serious side effects, including:

See "What is the most important information I should know about medicines called Nonsteroidal Anti-inflammatory Drugs (NSAIDs)"?

• new or worse high blood pressure

• heart failure

• liver problems including liver failure

• kidney problems including kidney failure

• low red blood cells (anemia)

• life-threatening skin reactions

• life threatening allergic reactions

• stomach pain, constipation, diarrhea, gas, heartburn, nausea, vomiting, and dizziness. Other side effects of NSAIDs include:

Get emergency help right away if you get any of the following symptoms:

•shortness of breath or trouble breathing

• slurred speech

• chest pain

• swelling of the face or throat

• weakness in one part or side of your body

Stop taking your NSAID and call your healthcare provider right away if you get any of the following symptoms:

• nausea

• vomit blood

• more tired or weaker than usual

• there is blood in your bowel movement or it is black and sticky like tar

• itching

• diarrhea

• unusual weight gain

• your skin or eyes look yellow

• skin rash or blisters with fever

• indigestion or stomach pain

• swelling of the arms and legs, hands and feet

• flu-like symptoms

If you take too much of your NSAID, call your healthcare provider or get medical help right away.

These are not all the possible side effects with NSAIDs. For more information, ask your healthcare provider or pharmacist about NSAIDs.

Call your doctor for medical advice about side effects. You may report side effects to FDA at 1-800-FDA-1088.

Other information about NSAIDs

• Aspirin is an NSAID but it does not increase the chance of a heart attack. Aspirin can cause bleeding in the brain, stomach, and intestines. Aspirin can also cause ulcers in the stomach and intestines.

• Some NSAIDs are sold in lower doses without a prescription (over-the-counter). Talk to your healthcare provider before using over-the-counter NSAIDs for more than 10 days.

General information about the safe and effective use of NSAIDs

Medicines are sometimes prescribed for purposes other than those listed in a Medication Guide. Do not use NSAIDs for a condition for which it was not prescribed. Do not give NSAIDs to other people, even if they have the same symptoms that you have. It may harm them.

If you would like more information about NSAIDs, talk with your healthcare provider. You can ask your pharmacist or healthcare provider for information about NSAIDs that is written for health professionals.

Manufactured by:

KVK-TECH INC.

110 Terry Drive

Newtown, PA 18940

Item ID # 006030/06

Manufacturer’s Code: 10702 07/15

For more information, go to or call our customer service at 215-579-1842. www.kvktech.com

This Medication Guide has been approved by the U.S. Food and Drug Administration.